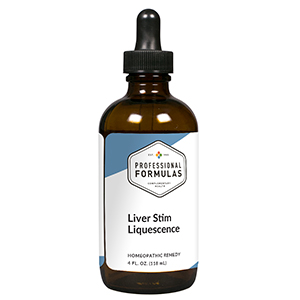 DRUG LABEL: Liver Stim Liquescence
NDC: 63083-3015 | Form: LIQUID
Manufacturer: Professional Complementary Health Formulas
Category: homeopathic | Type: HUMAN OTC DRUG LABEL
Date: 20190815

ACTIVE INGREDIENTS: BETA VULGARIS WHOLE 2 [hp_X]/118 mL; MILK THISTLE 2 [hp_X]/118 mL; CHELIDONIUM MAJUS WHOLE 2 [hp_X]/118 mL; LYCOPODIUM CLAVATUM SPORE 2 [hp_X]/118 mL; TARAXACUM OFFICINALE 2 [hp_X]/118 mL; ARCTOSTAPHYLOS TOMENTOSA WHOLE 2 [hp_X]/118 mL; DAIKON 3 [hp_X]/118 mL; GOLDENSEAL 5 [hp_X]/118 mL; BOS TAURUS BILE 6 [hp_X]/118 mL; BOS TAURUS GALLBLADDER 6 [hp_X]/118 mL; BEEF LIVER 6 [hp_X]/118 mL; SODIUM SULFATE 6 [hp_X]/118 mL; PHOSPHORUS 6 [hp_X]/118 mL; PICRORHIZA KURROA WHOLE 6 [hp_X]/118 mL; PTELEA TRIFOLIATA BARK 6 [hp_X]/118 mL
INACTIVE INGREDIENTS: ALCOHOL; WATER

T15

ACTIVE INGREDIENTS

Beta vulgaris 2X
Carduus marianus 2X
Chelidonium majus 2X
Lycopodium clavatum 2X
Taraxacum officinale 2X
Uva-ursi 2X
Raphanus sativus 3X
Hydrastis canadensis 5X
Fel tauri 6X
Gallbladder 6X
Liver 6X
Natrum sulphuricum 6X
Phosphorus 6X
Picrorrhiza kurroa 6X
Ptelea trifoliata 6X

QUESTIONS

Professional Formulas

PO Box 2034 Lake Oswego, OR 97035

INDICATIONS

For the temporary relief of minor abdominal pain or swelling, fatigue, irritability, constipation, loss of appetite, or low energy level.*

PURPOSE

*Claims based on traditional homeopathic practice, not accepted medical evidence. Not FDA evaluated.

WARNINGS

Severe or persistent symptoms may be serious. Consult a doctor promptly. Keep out of the reach of children. In case of overdose, get medical help or contact a poison control center right away. If pregnant or breastfeeding, ask a healthcare professional before use.

Keep out of the reach of children.

PREGNANCY OR BREAST FEEDING

If pregnant or breastfeeding, ask a healthcare professional before use.

DIRECTIONS

Place drops under tongue 30 minutes before/after meals. Adults and children 12 years and over: Take one full dropper up to 2 times per day. Consult a physician for use in children under 12 years of age.

OTHER INFORMATION

Tamper resistant. If seal is broken, do not use. After opening, close container tightly and store at room temperature away from heat.

INACTIVE INGREDIENTS

20% ethanol, purified water.

LABEL

Est 1985

Professional Formulas

Complementary Health

Liver Stim Liquescence

Homeopathic Remedy

4 FL. OZ. (118 mL)